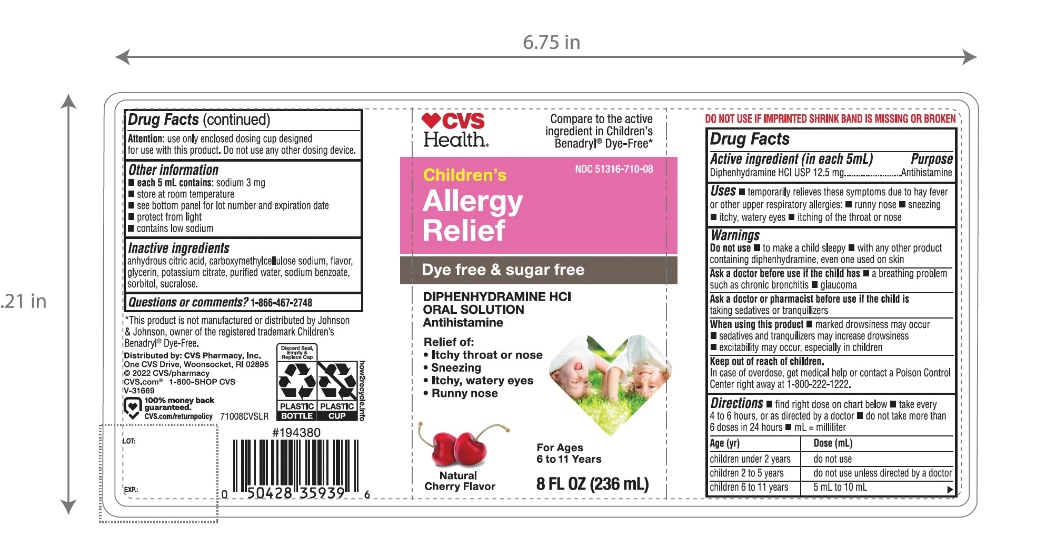 DRUG LABEL: CVS dye-free childrens allergy
NDC: 51316-710 | Form: SYRUP
Manufacturer: CVS PHARMACY
Category: otc | Type: HUMAN OTC DRUG LABEL
Date: 20251209

ACTIVE INGREDIENTS: DIPHENHYDRAMINE HYDROCHLORIDE 12.5 mg/5 mL
INACTIVE INGREDIENTS: ANHYDROUS CITRIC ACID; CARBOXYMETHYLCELLULOSE SODIUM, UNSPECIFIED; GLYCERIN; POTASSIUM CITRATE; WATER; SODIUM BENZOATE; SORBITOL; SUCRALOSE

Active ingredient (in each 5 mL)

Diphenhydramine HCl USP 12.5 mg

Purpose

Antihistamine

Uses

- temporarily relieves these symptoms due to hay fever or other upper respiratory allergies:
  - runny nose
  - sneezing
  - itchy, watery eyes
  - itching of the nose or throat

Warnings

Do not use

- to make a child sleepy
- with any other product containing diphenhydramine, even one used on skin

Ask a doctor before use if the child has

- a breathing problem such as chronic bronchitis
- glaucoma

Ask a doctor or pharmacist before use if the child istaking sedatives or tranquilizers

When using this product

- marked drowsiness may occur
- sedatives and tranquilizers may increase drowsiness
- excitability may occur, especially in children

Keep out of reach of children.

In case of overdose, get medical help or contact a Poison Control Center right away. (1-800-222-1222)

Directions

- find right dose on chart below
- take every 4 to 6 hours, or as directed by a doctor
- do not take more than 6 doses in 24 hours
- mL = milliliter

Age (yr) | Dose (mL)
children under 2 years | do not use
children 2 to 5 years | do not use unless directed by a doctor
children 6 to 11 years | 5 mL to 10 mL

Attention:use only enclosed dosing cup designed for use with this product. Do not use any other dosing device.

Other information

- each 5 mL contains: sodium 3 mg
- store at room temperature
- protect from sunlight
- see bottom panel for lot number and expiration date
- contains low sodium

Inactive ingredients

anhydrous citric acid, carboxymethylcellulose sodium, flavors, glycerin, potassium citrate, purified water, sodium benzoate, sorbitol, sucralose.

Questions or comments?

1-866-467-2748

PRINCIPAL DISPLAY PANEL

NDC 51316-710-08

*Compare to theactive ingredient in Children's Benadryl® Dye-Free*

Dye-Free

Children’s Allergy Relief

Diphenhydramine HCl l Antihistamine

Oral Solution

For Relief Of:

- Runny nose
- sneezing
- itchy, watery eyes
- Itchy Throat or Nose

Sugar Free

Natural Cherry Flavor

8 FL. OZ. (236 mL)

Distributed by:

*This product is not manufactured or distributed by Johnson & Johnson, owner of the registered trademark Children’s Benadryl® Dye –Free.